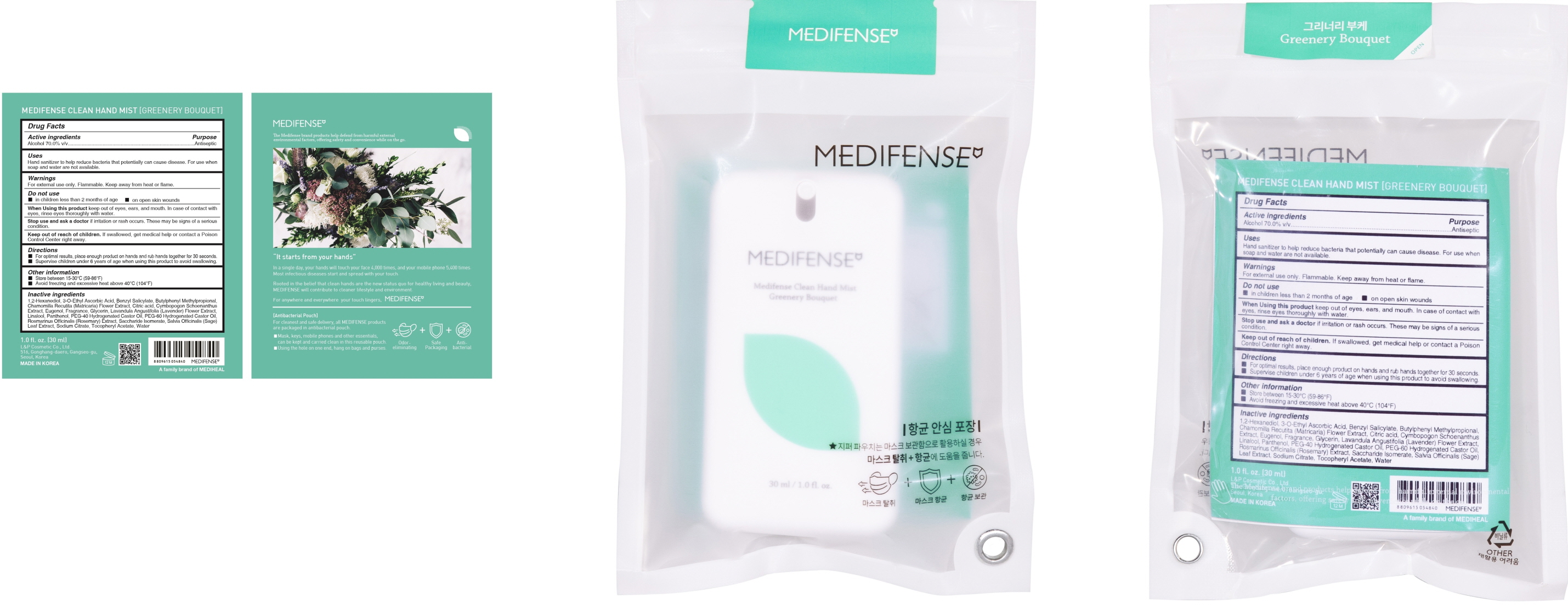 DRUG LABEL: MEDIFENSE CLEAN HAND MIST GREENERY BOUQUET
NDC: 74005-040 | Form: SPRAY
Manufacturer: L&P Cosmetic Co., Ltd.
Category: otc | Type: HUMAN OTC DRUG LABEL
Date: 20201119

ACTIVE INGREDIENTS: ALCOHOL 21 mL/30 mL
INACTIVE INGREDIENTS: 1,2-Hexanediol; 3-O-Ethyl Ascorbic Acid; Benzyl Salicylate; Butylphenyl Methylpropional; CHAMOMILE; CITRIC ACID MONOHYDRATE; CYMBOPOGON SCHOENANTHUS TOP; Eugenol; Glycerin; LAVANDULA ANGUSTIFOLIA SUBSP. ANGUSTIFOLIA FLOWER; LINALOOL, (+/-)-; Panthenol; POLYOXYL 40 HYDROGENATED CASTOR OIL; ROSEMARY; Saccharide Isomerate; SAGE; SODIUM CITRATE, UNSPECIFIED FORM; .ALPHA.-TOCOPHEROL ACETATE; Water

Active Ingredient(s)

ALCOHOL 70.0% v/v

Purpose

ANTISEPTIC

Warnings

For external use only. Flammable. Keep away from heat or flame
--------------------------------------------------------------------------------------------------------
Do not use
• in children less than 2 months of age
• on open skin wounds
--------------------------------------------------------------------------------------------------------
When using this product keep out of eyes, ears, and mouth. In case of contact with eyes, rinse eyes thoroughly with water.
--------------------------------------------------------------------------------------------------------
Stop use and ask a doctor if irritation or rash occurs. These may be signs of a serious condition.

Keep out of reach of children. If swallowed, get medical help or contact a Poison Control Center right away.

Uses

Hand sanitizer to help reduce bacteria that potentially can cause disease. For use when soap and water are not available.

Directions

• For optimal results, place enough product on hands and rub hands together for 30 seconds.
• Supervise children under 6 years of age when using this product to avoid swallowing.

Other information

• Store between 15-30C (59-86F)
• Avoid freezing and excessive heat above 40C (104F)

Inactive ingredients

1,2-Hexanediol, 3-O-Ethyl Ascorbic Acid, Benzyl Salicylate, Butylphenyl Methylpropional, Chamomilla Recutita (Matricaria) Flower Extract, Citric acid, Cymbopogon Schoenanthus Extract, Eugenol, Fragrance, Glycerin, Lavandula Angustifolia (Lavender) Flower Extract, Linalool, Panthenol, PEG-40 Hydrogenated Castor Oil, PEG-60 Hydrogenated Castor Oil, Rosmarinus Officinalis (Rosemary) Extract, Saccharide Isomerate, Salvia Officinalis (Sage) Leaf Extract, Sodium Citrate, Tocopheryl Acetate, Water